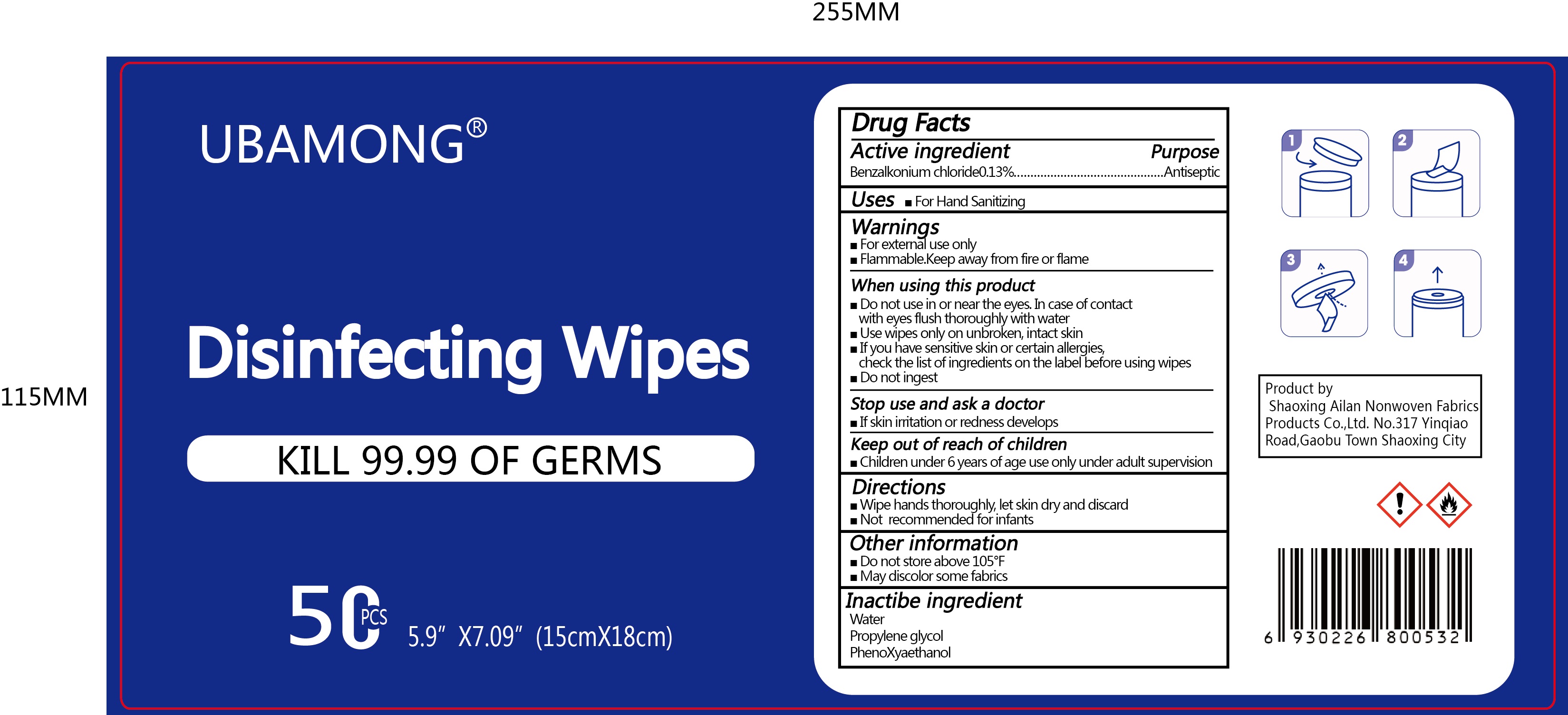 DRUG LABEL: UBAMONG Disinfecting Wipes
NDC: 80002-001 | Form: CLOTH
Manufacturer: Shaoxing Ailan Non-Woven Fabric Products Co., Ltd.
Category: otc | Type: HUMAN OTC DRUG LABEL
Date: 20200812

ACTIVE INGREDIENTS: BENZALKONIUM CHLORIDE 0.13 g/100 g
INACTIVE INGREDIENTS: WATER; PROPYLENE GLYCOL; PHENOXYETHANOL

80002-001 UBAMONG Disinfecting Wipes 0.13% BENZALKONIUM CHLORIDE

Active Ingredient

Benzalkonium Chloride 0.13%

Purpose

Antiseptic

USE

For Hand Sanitizing

Warning

■For external use only
■Flammable. Keep away from fire or flame
When using this product
■Do not use in or near the eyes. In case of contact
with eyes flush thoroughly with water
■Use wipes only on unbroken, intact skin
■If you have sensitive skin or certain allergies,
check the list of ingredients on the label before using wipes
■Do not ingest
Stop use and ask a doctor
■If skin irritation or redness develops

Keep out of reach of children
■Children under 6 years of age use only under adult supervision

Directions

■Wipe hands thoroughly, let skin dry and discard
■Not recommended for infants

Inactive ingredients

Aqua, Propylene Glycol, Phenoxyethanol.